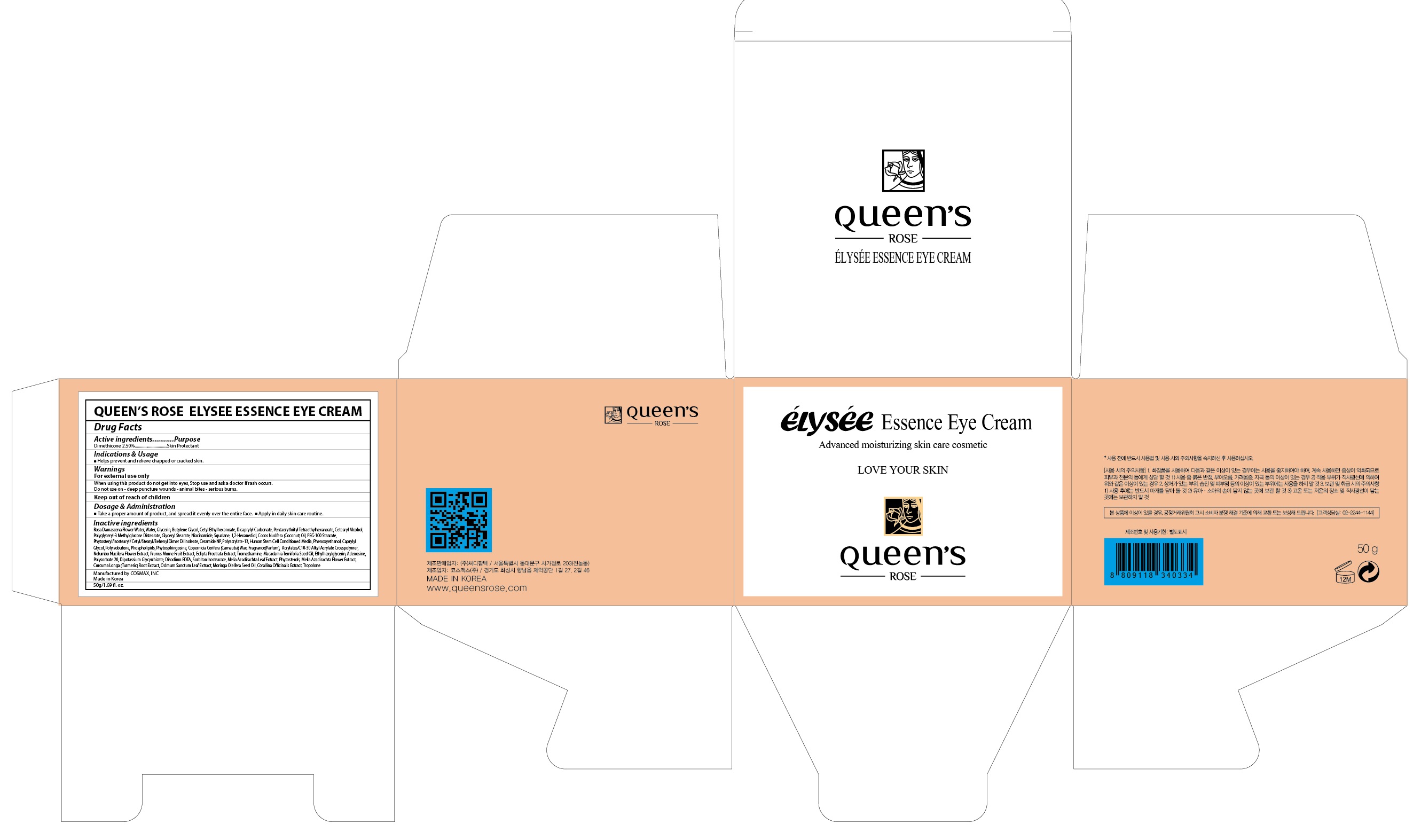 DRUG LABEL: QUEENS ROSE ELYSEE ESSENCE EYE
NDC: 71252-070 | Form: CREAM
Manufacturer: Cdpharmtec Co.,ltd
Category: otc | Type: HUMAN OTC DRUG LABEL
Date: 20170324

ACTIVE INGREDIENTS: Dimethicone 1.25 g/50 g
INACTIVE INGREDIENTS: ROSA DAMASCENA FLOWER OIL; Water

ACTIVE INGREDIENT

Active ingredients: Dimethicone 2.50%

INACTIVE INGREDIENT

Inactive ingredients: Rosa Damascena Flower Water, Water, Glycerin, Butylene Glycol, Cetyl Ethylhexanoate, Dicaprylyl Carbonate, Pentaerythrityl Tetraethylhexanoate, Cetearyl Alcohol, Polyglyceryl-3 Methylglucose Distearate, Glyceryl Stearate, Niacinamide, Squalane, 1,2-Hexanediol, Cocos Nucifera (Coconut) Oil, PEG-100 Stearate, Phytosteryl/Isostearyl/Cetyl/Stearyl/Behenyl Dimer Dilinoleate, Ceramide NP, Polyacrylate-13, Human Stem Cell Conditioned Media, Phenoxyethanol, Caprylyl Glycol, Polyisobutene, Phospholipids,Phytosphingosine, Copernicia Cerifera (Carnauba) Wax, Fragrance(Parfum), Acrylates/C10-30 Alkyl Acrylate Crosspolymer, Nelumbo Nucifera Flower Extract, Prunus Mume Fruit Extract, Eclipta Prostrata Extract, Tromethamine, Macadamia Ternifolia Seed Oil, Ethylhexylglycerin, Adenosine, Polysorbate 20, Dipotassium Glycyrrhizate, Disodium EDTA, Sorbitan Isostearate, Melia Azadirachta Leaf Extract, Phytosterols, Melia Azadirachta Flower Extract, Curcuma Longa (Turmeric) Root Extract, Ocimum Sanctum Leaf Extract, Moringa Oleifera Seed Oil, Corallina Officinalis Extract, Tropolone

PURPOSE

Purpose: Skin Protectant

WARNINGS

Warnings: For external use only When using this product do not get into eyes, Stop use and ask a doctor if rash occurs. Do not use on - deep puncture wounds - animal bites - serious burns.

KEEP OUT OF REACH OF CHILDREN

INDICATIONS & USAGE

Indications & Usage: Helps prevent and relieve chapped or cracked skin.

DOSAGE & ADMINISTRATION

Dosage & Administration: - Take a proper amount of product, and spread it evenly over the entire face. - Apply in daily skin care routine.